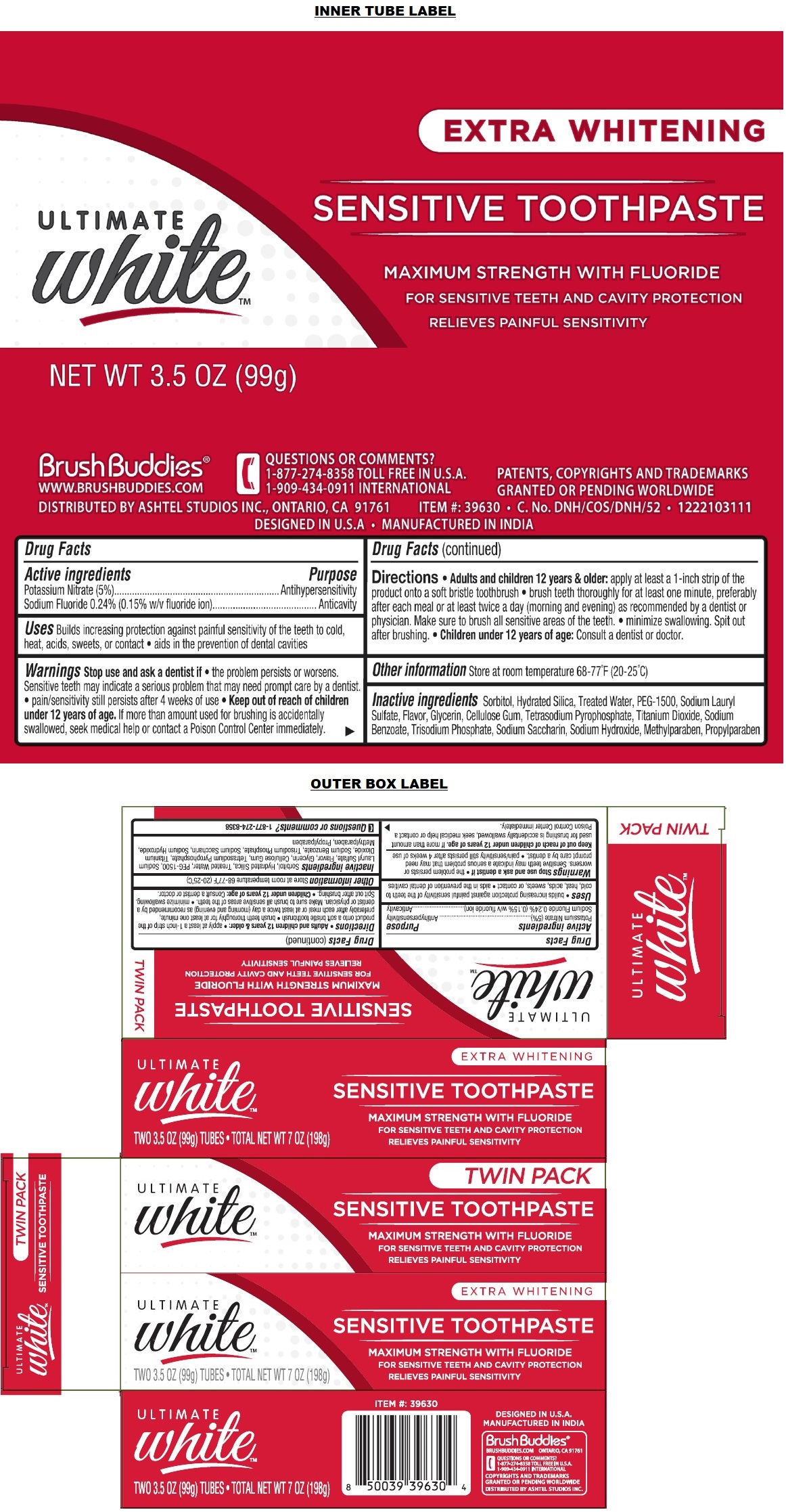 DRUG LABEL: Ultimate White Sensitive Whitening
NDC: 70108-075 | Form: PASTE, DENTIFRICE
Manufacturer: Ashtel Studios, Inc.
Category: otc | Type: HUMAN OTC DRUG LABEL
Date: 20230328

ACTIVE INGREDIENTS: POTASSIUM NITRATE 5 g/100 g; SODIUM FLUORIDE 0.24 g/100 g
INACTIVE INGREDIENTS: SORBITOL; HYDRATED SILICA; WATER; POLYETHYLENE GLYCOL 1600; SODIUM LAURYL SULFATE; GLYCERIN; CARBOXYMETHYLCELLULOSE SODIUM, UNSPECIFIED; SODIUM PYROPHOSPHATE; TITANIUM DIOXIDE; SODIUM BENZOATE; SODIUM PHOSPHATE, TRIBASIC, ANHYDROUS; SACCHARIN SODIUM; SODIUM HYDROXIDE; METHYLPARABEN; PROPYLPARABEN

ULTIMATE whiteTM SENSITIVE TOOTHPASTE

Active ingredients

Potassium Nitrate (5%)
Sodium Fluoride 0.24% (0.15% w/v fluoride ion)

Purpose

Antihypersensitivity
Anticavity

Uses

• builds increasing protection against painful sensitivity of the teeth to cold, heat, acids, sweets, or contact • aids in the prevention of dental cavities

Warnings

Stop use and ask a dentist if • the problem persists or worsens. Sensitive teeth may indicate a serious problem that may need prompt care by a dentist. • pain/sensitivity still persists after 4 weeks of use

Keep out of reach of children under 12 years of age. If more than amount used for brushing is accidentally swallowed, seek medical help or contact a Poison Control Center immediately.

Directions

• Adults and children 12 years & older: • apply at least a 1-inch strip of the product onto a soft bristle toothbrush • brush teeth thoroughly for at least one minute, preferably after each meal or at least twice a day (morning and evening) as recommended by a dentist or physician. Make sure to brush all sensitive areas of the teeth. • minimize swallowing. Spit out after brushing. • Children under 12 years of age: Consult a dentist or doctor.

Other information

Store at room temperature 68-77°F (20-25°C)

Inactive ingredients

Sorbitol, Hydrated Silica, Treated Water, PEG-1500, Sodium Lauryl Sulfate, Flavor, Glycerin, Cellulose Gum, Tetrasodium Pyrophosphate, Titanium Dioxide, Sodium Benzoate, Trisodium Phosphate, Sodium Saccharin, Sodium Hydroxide, Methylparaben, Propylparaben

Questions or comments?

1-877-274-8358

TWIN PACK

SENSITIVE TOOTHPASTE

MAXIMUM STRENGTH WITH FLUORIDE

FOR SENSITIVE TEETH AND CAVITY PROTECTION
RELIEVES PAINFUL SENSITIVITY

EXTRA WHITENING

DESIGNED IN U.S.A.
MANUFACTURED IN INDIA

Brush Buddies®
BRUSHBUDDIES.COM ONTARIO, CA 91761

QUESTIONS OR COMMENTS?
1-877-274-8358 TOLL FREE IN U.S.A.
1-909-434-0911 INTERNATIONAL

COPYRIGHTS AND TRADEMARKS GRANTED OR PENDING WORLDWIDE
DISTRIBUTED BY ASHTEL STUDIOS INC.